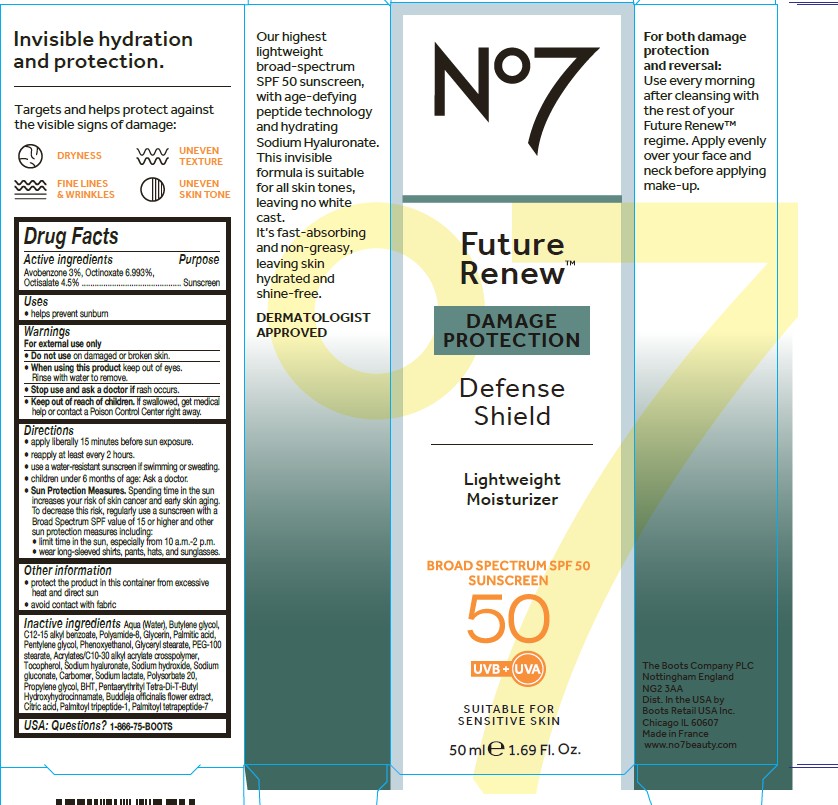 DRUG LABEL: No7 Future Renew Defense Shield SPF 50
NDC: 61589-9301 | Form: CREAM
Manufacturer: BCMC
Category: otc | Type: HUMAN OTC DRUG LABEL
Date: 20250722

ACTIVE INGREDIENTS: AVOBENZONE 3 g/50 g; OCTINOXATE 6.993 g/50 g; OCTISALATE 4.5 g/50 g
INACTIVE INGREDIENTS: WATER; BUTYLENE GLYCOL; GLYCERIN; C12-15 ALKYL BENZOATE; POLYAMIDE-8 (4500 MW); PALMITIC ACID; PENTYLENE GLYCOL; PHENOXYETHANOL; GLYCERYL STEARATE SE; PEG-100 STEARATE; ACRYLATES/C10-30 ALKYL ACRYLATE CROSSPOLYMER (60000 MPA.S); TOCOPHEROL; SODIUM HYALURONATE; SODIUM HYDROXIDE; SODIUM GLUCONATE; CARBOMER; SODIUM LACTATE; POLYSORBATE 20; PROPYLENE GLYCOL; BHT; PENTAERYTHRITYL TETRA-DI-T-BUTYL HYDROXYHYDROCINNAMATE; BUDDLEJA OFFICINALIS FLOWER; PALMITOYL TRIPEPTIDE-1; CITRIC ACID ACETATE; PALMITOYL TETRAPEPTIDE-7; BENZYL BENZOATE; BENZYL ALCOHOL

No7 Future Renew Damage Protection Defense Shield SPF 50

Carton Active Ingredients Section

Active ingredients

Avobenzone 3%

Octinoxate 0.5%

Octisalate 5%

Octocrylene 7.5%

Uses

Uses - helps prevent sunburn

Ask a doctor

Stop use and ask a doctor if rash occurs

Keep out of reach of children

If swallowed, get medical help or contact a Poison Control Center right away

Storage

Other information

protect the product in this container from excessive heat and direct sun

avoid contact with fabrics

Inactive ingredients

Aqua (Water), Dibutyl adipate, Glycerin, Polyglyceryl-3 methylglucose distearate, VP/eicosene copolymer, Capryloyl glycerin/sebacic acid copolymer, Tribehenin, Niacinamide, Dimethicone, Ammonium acryloyldimethyltaurate/VP copolymer, Butyrospermum parkii (Shea) butter, Tocopheryl acetate, Phenoxyethanol, Panthenol, Potassium cetyl phosphate, Caprylyl glycol, Parfum (fragrance), Dimethiconol, Sodium Benzoate, Sodium Hyaluronate, Ethylhexylglycerin, Hydrolyzed rice protein, Propylene glycol, Dipropylene glycol, Ascorbyl glucoside, Citric acid, Tetrasodium EDTA, T-butyl alcohol, Propanediol, Pentylene Glycol, Decyl glucoside, Morus alba leaf extract, BHT, Palmitoyl tetrapeptide-94, Palmitoyl tetrapeptide-95

PATIENT COUNSELING INFORMATION

USA: Questions? 1-866-75-BOOTS

The Boots Company PLC Nottingham England NG2 3AA

Boots Retail Ireland Dublin 12 Ireland

Dist. in the USA by Boots Retail USA Inc. New York NY 10007

Made in the UK

www.no7beauty.com

uses

Uses - helps prevent sunburn

Warnings

For external use only
● Do not use on damaged or broken skin.
● When using this product keep out of eyes.
Rinse with water to remove.
● Stop use and ask a doctor if rash occurs.
● Keep out of reach of children. If swallowed, get medical
help or contact a Poison Control Center right away

instructions

Apply evenly